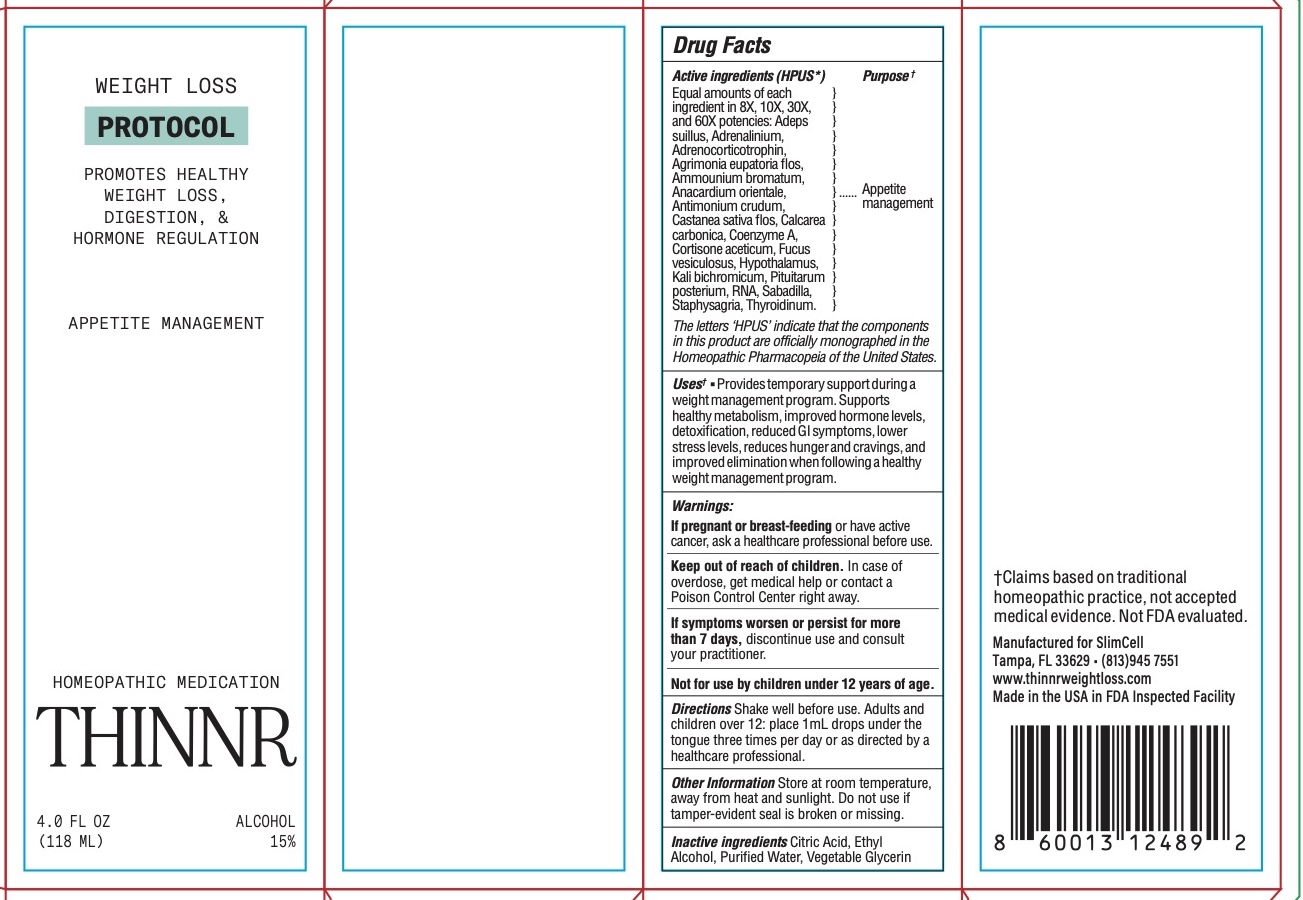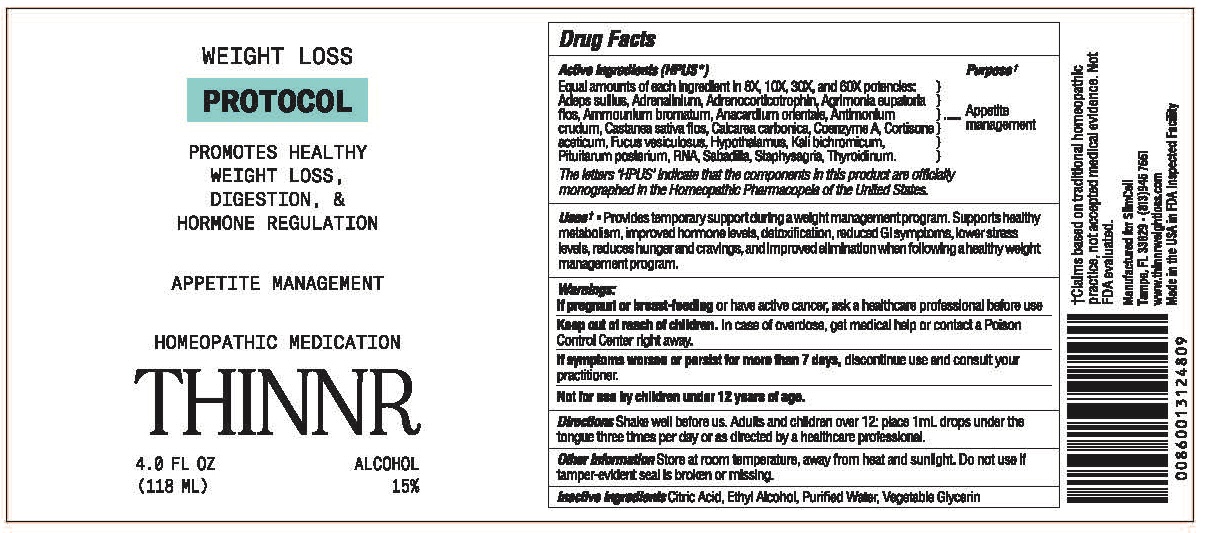 DRUG LABEL: Thinnr PROTOCOL
NDC: 85095-100 | Form: LIQUID
Manufacturer: SLIMCELL, LLC
Category: homeopathic | Type: HUMAN OTC DRUG LABEL
Date: 20250820

ACTIVE INGREDIENTS: CASTANEA SATIVA FLOWER 8 [hp_X]/1 mL; ADEPS SUILLUS 8 [hp_X]/1 mL; SEMECARPUS ANACARDIUM JUICE 8 [hp_X]/1 mL; AMMONIUM BROMIDE 8 [hp_X]/1 mL; AGRIMONIA EUPATORIA FLOWER 8 [hp_X]/1 mL; CORTICOTROPIN 8 [hp_X]/1 mL; EPINEPHRINE 8 [hp_X]/1 mL; POTASSIUM DICHROMATE 8 [hp_X]/1 mL; COENZYME A 8 [hp_X]/1 mL; THYROID, UNSPECIFIED 8 [hp_X]/1 mL; ANTIMONY TRISULFIDE 8 [hp_X]/1 mL; OYSTER SHELL CALCIUM CARBONATE, CRUDE 8 [hp_X]/1 mL; CORTISONE ACETATE 8 [hp_X]/1 mL; FUCUS VESICULOSUS 8 [hp_X]/1 mL; BOS TAURUS HYPOTHALAMUS 8 [hp_X]/1 mL; SUS SCROFA PITUITARY GLAND, POSTERIOR 8 [hp_X]/1 mL; SACCHAROMYCES CEREVISIAE RNA 8 [hp_X]/1 mL; DELPHINIUM STAPHISAGRIA SEED 8 [hp_X]/1 mL; SCHOENOCAULON OFFICINALE SEED 8 [hp_X]/1 mL
INACTIVE INGREDIENTS: CITRIC ACID; ALCOHOL; WATER; GLYCERIN

Thinnr PROTOCOL

HPUS Active Ingredients: Equal amounts of each ingredient in 8X, 10X, 30X, and 60X potencies: Adeps suillus, Adrenalinium, Adrenocorticotrophin, Agrimonia eupatoria flos, Ammounium bromatum, Anacardium orientale, Antimonium crudum, Castanea sativa flos, Calcarea carbonica, Coenzyme A, Cortisone aceticum, Fucus vesiculosus, Hypothalamus, Kali bichromicum, Pituitarum posterium, RNA, Sabadilla, Staphysagria, Thyroidinum.

Uses*:

Uses*: Provides temporary support during a weight management program. Supports healthy metabolism, improved hormone levels, detoxification, lower stress levels, reduces hunger and cravings, and improved elimination when following a healthy weight management program.

Warnings

Warnings: If symptoms worsen or persist for more than 7 days, discontinue use and consult your practitioner.

Directions

Shake well before us. Adults and children over 12: place 1mL drops under the tongue three times per day or as directed by a healthcare professional.

Other Information

Store at room temperature, away from heat and sunlight.
Do not use if tamper-evident seal is broken or missing.

Inactive Ingredients

Inactive Ingredients: Ethyl Alcohol, Glycerin, Purified Water.

Keep out of reach of children. In case of overdose, get medical help or contact a Poison Control Center right away.

If pregnant or breast-feeding or have active cancer, ask a healthcare professional before use

PURPOSE

Appetite management